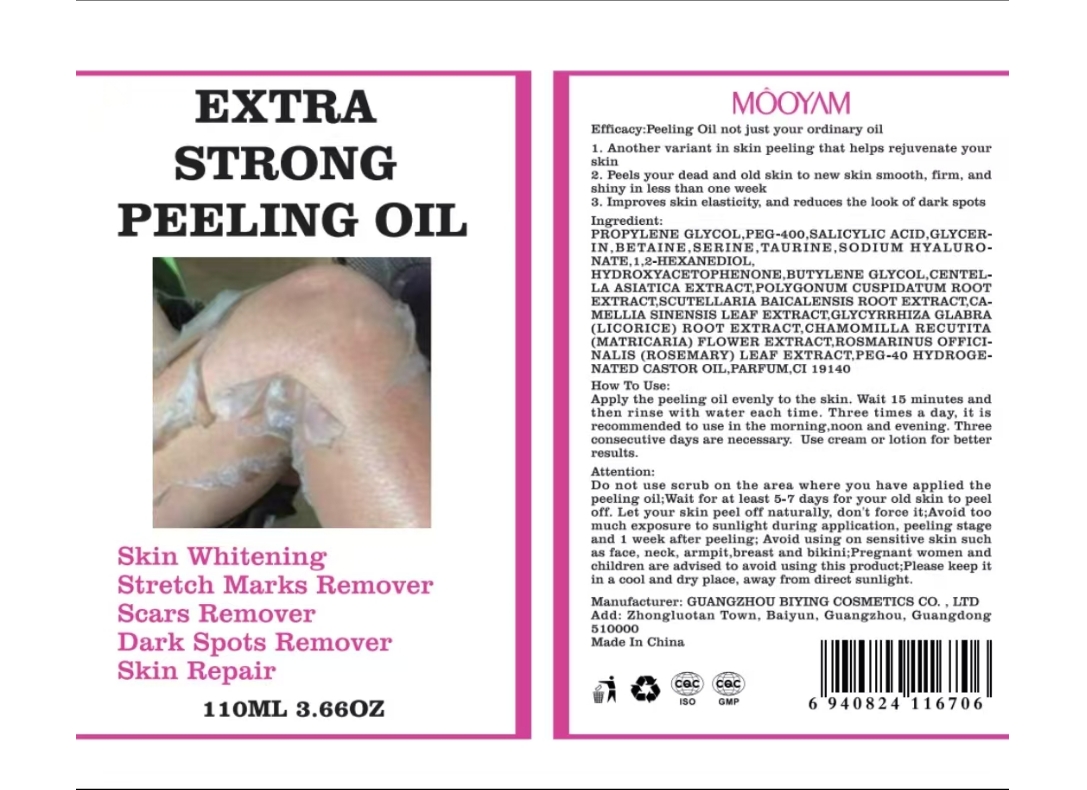 DRUG LABEL: MOOYAM PEELING SOLUTIONS
NDC: 84507-026 | Form: OIL
Manufacturer: Guangdong Miaolian Cosmetics Co., Ltd.
Category: otc | Type: HUMAN OTC DRUG LABEL
Date: 20241224

ACTIVE INGREDIENTS: SALICYLIC ACID 1.9 mg/100 mL
INACTIVE INGREDIENTS: SCUTELLARIA BAICALENSIS ROOT; AQUA; PROPYLENE GLYCOL; PEG-40 HYDROGENATED CASTOR OIL; PEG-10; MATRICARIA RECUTITA; PEG-400; FRAGRANCE FLORAL ORC0902236; SODIUM CHLORIDE; ROSMARINUS OFFICINALIS (ROSEMARY) LEAF OIL; CENTELLA ASIATICA; POLYGONUM CUSPIDATUM ROOT; GLYCYRRHIZA GLABRA (LICORICE) RHIZOME/ROOT; CI 19140; CI 15985; BUTYLENE GLYCOL; CAMELLIA SINENSIS LEAF

DOSAGE AND ADMINISTRATION

Apply once daily to clean face and neck, avoiding the eye area

WARNINGS

Risk InformationFor external use only
Mention de risquesPour usage externe seulement
Do not use on damaged or broken skin.
Ne pas utiliser sur la peau endommagée ou avec des lésions
If rash occurs, discontinue use and consult a health care practitioner.
En présence d'une éruption cutanée, cesser l'utilisation et consulter un praticien de soins de santé
When using this product keep out of eyes. Rinse with water to remove.
Eviter tout contact avec les yeux. Rincer a l'eau le cas échéant
Keep out of reach of children. If swallowed, get medical help or contact a Poison Control Center right away.

INACTIVE INGREDIENT

AQUA
PROPYLENE GLYCOL
PEG-400
PEG-40 HYDROGENATED CASTOR OIL
PEG-10
FRAGRANCE
CI 19140
SODIUM CHLORIDE
CI 15985
BUTYLENE GLYCOL
CENTELLA ASIATICA EXTRACT
POLYGONUM CUSPIDATUM ROOT EXTRACT
SCUTELLARIA BAICALENSIS ROOT EXTRACT
CAMELLIA SINENSIS LEAF EXTRACT
GLYCYRRHIZA GLABRA (LICORICE) ROOT EXTRACT
CHAMOMILLA RECUTITA (MATRICARIA) FLOWER EXTRACT
ROSMARINUS OFFICINALIS (ROSEMARY) LEAF EXTRACT

INDICATIONS AND USAGE

1. Removes Dead Skin Cells
Exfoliating peeling oil helps dissolve and peel away dead skin cells on the surface of the skin, promoting cell turnover and leaving the skin smoother and more radiant.
2. Enhances Absorption
After exfoliation, the skin’s surface is free from obstructions, allowing it to better absorb active ingredients from subsequent skincare products such as serums and moisturizers, boosting their effectiveness.

Keep out of reach of children. If swallowed, get medical help or contact a Poison Control Center right away.

PURPOSE

1. Removes Dead Skin Cells
Exfoliating peeling oil helps dissolve and peel away dead skin cells on the surface of the skin, promoting cell turnover and leaving the skin smoother and more radiant.
2. Enhances Absorption
After exfoliation, the skin’s surface is free from obstructions, allowing it to better absorb active ingredients from subsequent skincare products such as serums and moisturizers, boosting their effectiveness.

ACTIVE INGREDIENT

SALICYLIC ACID ------1.9%